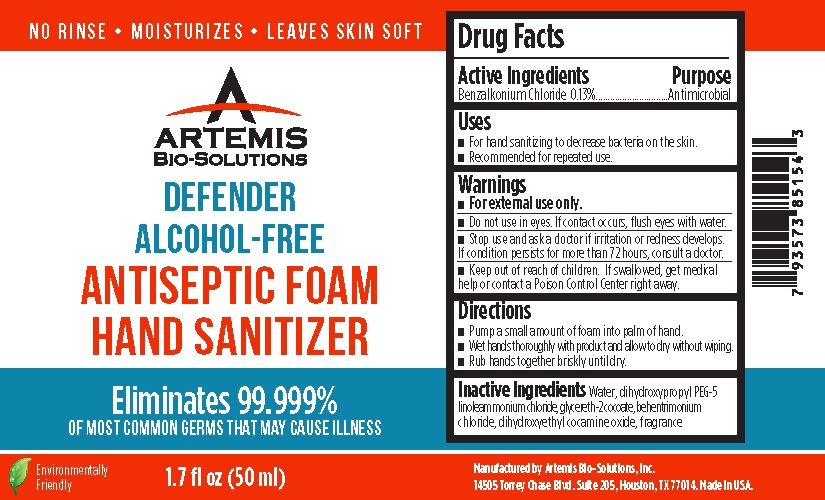 DRUG LABEL: ARTEMIS  Alcohol-Free Antiseptic Foam Hand Sanitizer
NDC: 49765-310 | Form: LIQUID
Manufacturer: Artemis Bio-Solutions, Inc.
Category: otc | Type: HUMAN OTC DRUG LABEL
Date: 20200710

ACTIVE INGREDIENTS: BENZALKONIUM CHLORIDE 1.3 mg/100 mL
INACTIVE INGREDIENTS: WATER; DIHYDROXYPROPYL PEG-5 LINOLEAMMONIUM CHLORIDE; GLYCERETH-2 COCOATE; BEHENTRIMONIUM CHLORIDE; DIHYDROXYETHYL COCAMINE OXIDE

ARTEMIS ALCOHOL-FREE Antiseptic Foam Hand Sanitizer

Drug Facts

Active Ingredients

Benzalkonium Chloride 0.13%

Purpose

Antimicrobial

Uses

- For hand sanitizing to decrease bacteria on the skin
- Recommended for repeated use

Warnings

- For external use only.

- Do not use in eyes. If contact occurs, flush eyes with water.

- Stop use and ask a doctor if irritation or redness develops. If condition persists for more than 72 hours, consult a doctor.

- Keep out of reach of children. If swallowed, get medical help or contact a Poison Control Center right away.

Directions

- Pump a small amount of foam into palm of hand.
- Wet hands thoroughly with product and allow to dry without wiping.
- Rub hands together briskly until dry.

Inactive Ingredients

Water, dihydroxypropyl PEG-5 linoleammonium chloride, glycereth-2cocoate, behentrimonium chloride, dihydroxyethyl cocamine oxide, fragrance

ARTEMIS BIOSOLUTIONS

Manufactured by Artemis BioSolutions.

960 N. Industrial Dr., Ste.4 Elmhurst, IL 60126.

Made in USA.